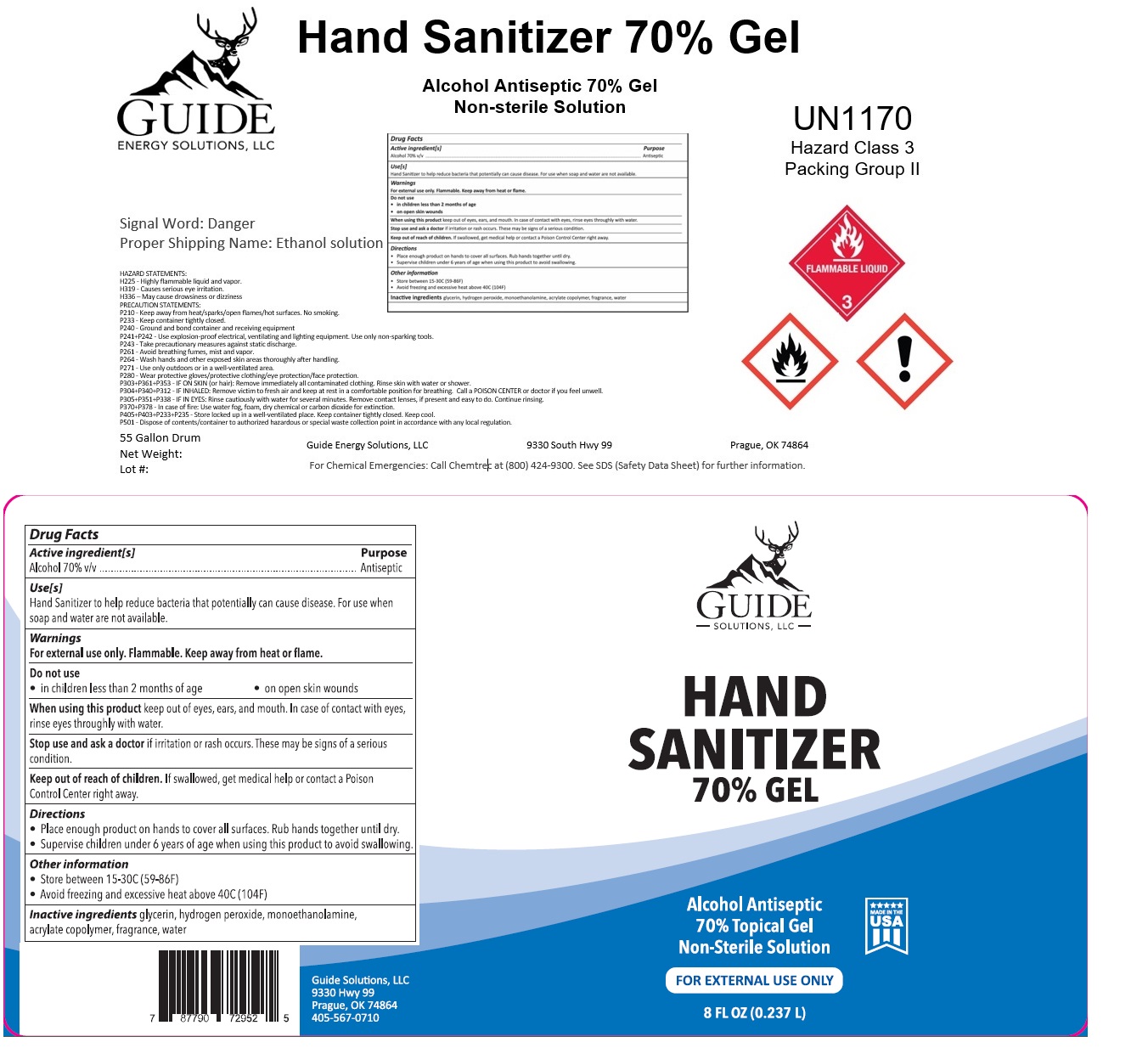 DRUG LABEL: Hand Sanitizer 70% Gel
NDC: 77042-770 | Form: GEL
Manufacturer: Guide Energy Solutions LLC
Category: otc | Type: HUMAN OTC DRUG LABEL
Date: 20200616

ACTIVE INGREDIENTS: ALCOHOL 70 L/100 L
INACTIVE INGREDIENTS: GLYCERIN; HYDROGEN PEROXIDE; MONOETHANOLAMINE; METHACRYLIC ACID - ETHYL ACRYLATE COPOLYMER (4500 MPA.S); WATER

Hand Sanitizer 70% Gel

Active ingredient[s]

Alcohol 70% v/v

Purpose

Antiseptic

Use[s]

Hand Sanitizer to help reduce bacteria that potentially can cause disease. For use when soap and water are not available.

Warnings

For external use only. Flammable. Keep away from heat or flame.

Do not use

• in children less than 2 months of age

• on open skin wounds

When using this product keep out of eyes, ears, and mouth. In case of contact with eyes, rinse eyes thoroughly with water.

Stop use and ask a doctor if irritation or rash occurs. These may be signs of a serious condition.

Keep out of reach of children. If swallowed, get medical help or contact a Poison Control Center right away.

Directions

• Place enough product on hands to cover all surfaces. Rub hands together until dry.

• Supervise children under 6 years of age when using this product to avoid swallowing.

Other information

• Store between 15-30°C (59-83°F)

• Avoid freezing and excessive heat above 40°C (104°F)

INACTIVE INGREDIENT

Inactive ingredients glycerin, hydrogen peroxide, monoethanolamine, acrylate copolymer, fragrance, water

Alcohol Antiseptic 70% Gel

Non-sterile Solution

UN1170

Hazard Class 3

Packing Group II

FLAMMABLE LIQUID

Signal Word: Danger

Proper Shipping Name: Ethanol solution

HAZARD STATEMENTS:
H225 - Highly flammable liquid and vapor.
H319 - Causes serious eye irritation.
H336 – May cause drowsiness or dizziness

PRECAUTION STATEMENTS:
P210 - Keep away from heat/sparks/open flames/hot surfaces. No smoking.
P233 - Keep container tightly closed.
P240 - Ground and bond container and receiving equipment
P241+P242 - Use explosion-proof electrical, ventilating and lighting equipment. Use only non-sparking tools.
P243 - Take precautionary measures against static discharge.
P261 - Avoid breathing fumes, mist and vapor.
P264 - Wash hands and other exposed skin areas thoroughly after handling.
P271 - Use only outdoors or in a well-ventilated area.
P280 - Wear protective gloves/protective clothing/eye protection/face protection.
P303+P361+P353 - IF ON SKIN (or hair): Remove immediately all contaminated clothing. Rinse skin with water or shower.
P304+P340+P312 - IF INHALED: Remove victim to fresh air and keep at rest in a comfortable position for breathing. Call a POISON CENTER or doctor if you feel unwell.
P305+P351+P338 - IF IN EYES: Rinse cautiously with water for several minutes. Remove contact lenses, if present and easy to do. Continue rinsing.
P370+P378 - In case of fire: Use water fog, foam, dry chemical or carbon dioxide for extinction.
P405+P403+P233+P235 - Store locked up in a well-ventilated place. Keep container tightly closed. Keep cool.
P501 - Dispose of contents/container to authorized hazardous or special waste collection point in accordance with any local regulation.

Guide Energy Solutions, LLC 9330 South Hwy 99 Prague, OK 74864

For Chemical Emergencies: Call Chemtrec at (800) 424-9300. See SDS (Safety Data Sheet) for further information.